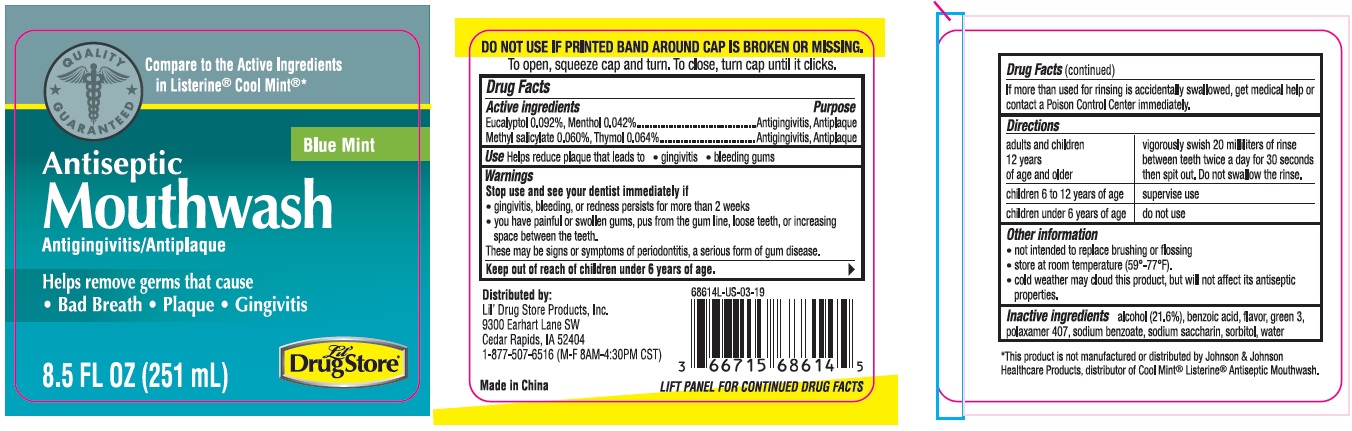 DRUG LABEL: Mouthwash
NDC: 71927-006 | Form: LIQUID
Manufacturer: Orazen Inc
Category: otc | Type: HUMAN OTC DRUG LABEL
Date: 20250407

ACTIVE INGREDIENTS: METHYL SALICYLATE 0.6 mg/1 mL; THYMOL 0.64 mg/1 mL; EUCALYPTOL 0.92 mg/1 mL; MENTHOL 0.42 mg/1 mL
INACTIVE INGREDIENTS: ALCOHOL; BENZOIC ACID; FD&C GREEN NO. 3; POLOXAMER 407; SODIUM BENZOATE; SACCHARIN SODIUM; SORBITOL; WATER

71927-006

Active ingredients
EUCALYPTOL 0.092%, MENTHOL 0.042%, METHYL SALICYLATE 0.060%, THYMOL 0.064%

Purpose
Antigingivitis, Antiplaque

Uses
Helps reduce plaque that leads to

- gingivitis
- bleeding gums

Warnings

Stop use and see your dentist immediately if

- gingivitis, bleeding or redness persists for more than 2 weeks
- you have painful or swollen gums, pus from the gum line, loose teeth, or increasing space between the teeth

These may be signs or symptoms of periodontitis, a serious form of gum disease.

Keep out of reach of children under 6 years of age . If more than used for rinsing is accidentally swallowed, get medical help or contact a Poison Control Center immediately.

Directions

adult and children 12 years of age and older | vigorously swish 20 millliliters of rinse between teeth twice a day for 30 seconds then spit out. Do not swallow the rinse.
children 6 to 20 years of age | supervise use
children uner 6 years of age | do not use

Other information

- not intended to replace brushing or flossing
- store at room temperature (59-77F)
- cold weather may cloud this product, but will not affect its antiseptic properties.

Inactive ingredients
alcohol (21.6%), benzoic acid, flavor, green 3, poloxamer 407, sodium benzoate, sodium saccharin, sorbitol, water